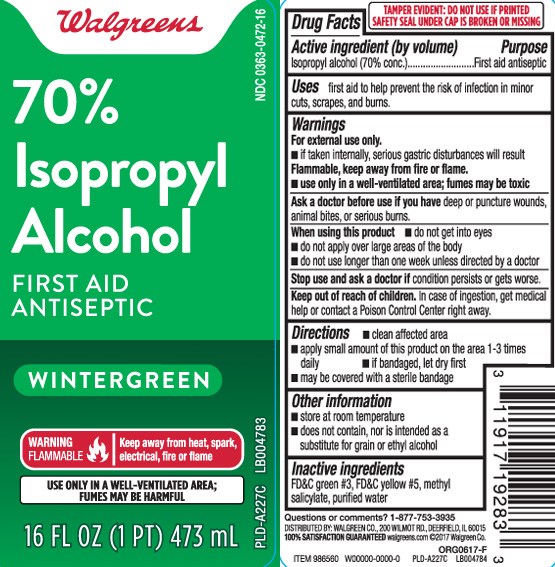 DRUG LABEL: Isopropyl alcohol
NDC: 0363-0472 | Form: LIQUID
Manufacturer: Walgreens
Category: otc | Type: HUMAN OTC DRUG LABEL
Date: 20250221

ACTIVE INGREDIENTS: ISOPROPYL ALCOHOL 70 mL/100 mL
INACTIVE INGREDIENTS: WATER; FD&C GREEN NO. 3; FD&C YELLOW NO. 5; METHYL SALICYLATE

Drug Facts

Active ingredient (by volume)

Isopropyl alcohol (70% conc.)

Purpose

First aid antiseptic

Uses

first aid to help prevent the risk of infection in minor cuts, scrapes, and burns.

Warnings

For external use only.

- If taken internaly, serious gastic disturbances will result

Flammable, keep away from fire or flame

- use only in a well-ventilated area; fumes may be toxic

Ask a doctor before use if you have

deep or puncture woods, animal bites or serious burns

When using this product

- do not get into eyes
- do not apply over large areas of the body
- do not use longer than one week unless directed by a doctor

Stop use and ask a doctor if

condition persists or gets worse

Keep out of reach of children.

In case of ingestion, get medical help or contact a Poison Control Center right away.

Directions

- clean affected area
- apply small amount of this product on the area 1-3 times daily
- if bandaged, let dry first
- may be covered with a sterile bandage

Other information

- store at room temperature
- does not contain, nor is intended as a substitute for grain or ethyl alcohol

Inactive ingredient

FD&C green #3, FD&C yellow #5, methyl salicylate, purified water

Principal Display Panel

70% Isopropyl Alcohol

FIRST AID ANTISEPTIC

WINTERGREEN

WARNING FLAMMABLE | keep away from heat, spark, electrical, fire or flame

USE ONLY IN A WELL-VENTILATED AREA; FUMES MAY BE HARMFUL

FL OZ (mL)

Questions or comments? 1-877-753-3935

TAMPER EVIDENT: DO NOT USE IF PRINTED SAFETY SEAL UNDER CAP IS BROKEN OR MISSING.

DISTRIBUTED BY: WALGREEN CO., 200 WILMOT RD., DEERFIELD, IL 60015

walgreens.com

Package Label

WALGREENS 70 % Isopropyl Alcohol Wintergreen